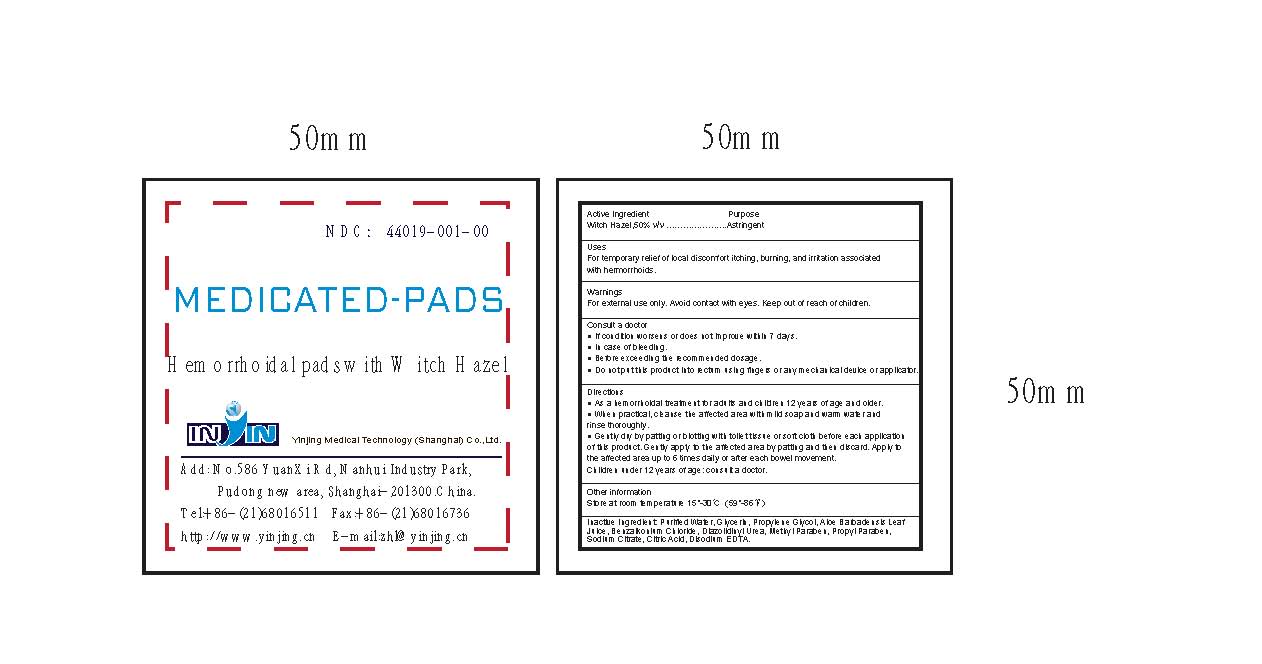 DRUG LABEL: MEDICATED-PADS Hemorrhoidal Pads with Witch Hazel
NDC: 44019-001 | Form: LIQUID
Manufacturer: Yinjing Medical Technology (Shanghai) Co., Ltd.
Category: otc | Type: HUMAN OTC DRUG LABEL
Date: 20171227

ACTIVE INGREDIENTS: WITCH HAZEL 50 g/100 g
INACTIVE INGREDIENTS: WATER; GLYCERIN; PROPYLENE GLYCOL; ALOE VERA LEAF; BENZALKONIUM CHLORIDE; DIAZOLIDINYL UREA; METHYLPARABEN; PROPYLPARABEN; SODIUM CITRATE; CITRIC ACID MONOHYDRATE; EDETATE DISODIUM

MEDICATED-PADS Hemorrhoidal Pads with Witch Hazel

Active ingredient

Witch Hazel,50% v/v

Purpose

Astringent

Use

For temporary relief of local discomfort itching, burning, and irritation associated with hermorrhoids.

Warnings

For external use only. Avoid contact with eyes.

Consult a doctor

- If condition worsens or does not improve within 7 days.
- In case of bleeding.
- Before exceeding the recommended dosage.
- Do not put this product into rectum using fingers or any mechanical device or applicator.

Directions

? As a hemorrhoidal treatment for adults and children 12 years of age and older.
? When practical, cleanse the affected area with mild soap and warm water and rinse thoroughly.
? Gently dry by patting or blotting with toilet tissue or soft cloth before each application of this product. Gently apply to the affected area by patting and then discard. Apply to the affected area up to 6 times daily or after each bowel movement. Children under 12 years of age: consult a doctor.

Other information

Store at room temperature 15^0 - 30^0 C (59^0 - 86^0 F)

Inactive Ingredients:

Purified Water, Glycerin, Propylene Glycol, Aloe Barbadensis Leaf Juice, Benzalkonium Chloride, Diazolidinyl Urea, Methyl Paraben, Propyl Paraben, Sodium Citrate, Citric Acid, Disodium EDTA.

PACKAGE LABEL

NDC: 44019-001-00

MEDICATED-PADS Hemorrhoidal pads with Witch Hazel IN IN Shanghai Medical Supplies Co.,Ltd. Add: No.586 YuanXi Rd, Nanhui Industry Park, Pudong new area, Shanghai-201300.China. Tel:+86-(21)68016511 Fax:+86-(21)68016736 http://www.yinjing.cn E-mail:zhl@yinjing.cn